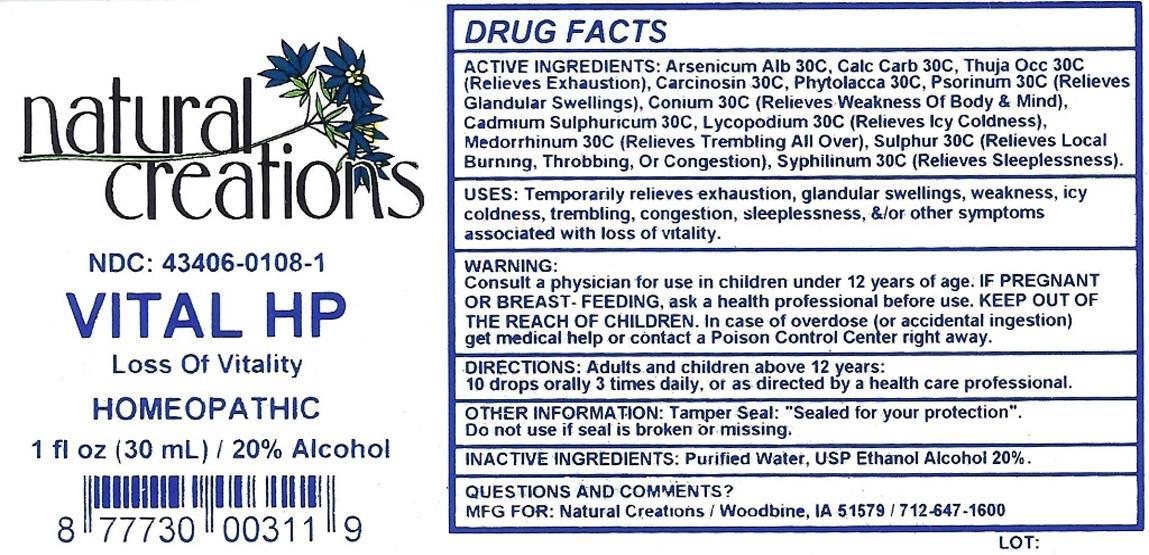 DRUG LABEL: VITAL HP
NDC: 43406-0108 | Form: LIQUID
Manufacturer: Natural Creations, Inc.
Category: homeopathic | Type: HUMAN OTC DRUG LABEL
Date: 20130107

ACTIVE INGREDIENTS: ARSENIC TRIOXIDE 30 [hp_C]/1 mL; CADMIUM SULFATE 30 [hp_C]/1 mL; OYSTER SHELL CALCIUM CARBONATE, CRUDE 30 [hp_C]/1 mL; HUMAN BREAST TUMOR CELL 30 [hp_C]/1 mL; CONIUM MACULATUM FLOWERING TOP 30 [hp_C]/1 mL; LYCOPODIUM CLAVATUM SPORE 30 [hp_C]/1 mL; GONORRHEAL URETHRAL SECRETION HUMAN 30 [hp_C]/1 mL; PHYTOLACCA AMERICANA ROOT 30 [hp_C]/1 mL; SCABIES LESION LYSATE (HUMAN) 30 [hp_C]/1 mL; SULFUR 30 [hp_C]/1 mL; TREPONEMIC SKIN CANKER HUMAN 30 [hp_C]/1 mL; THUJA OCCIDENTALIS LEAFY TWIG 30 [hp_C]/1 mL
INACTIVE INGREDIENTS: WATER; ALCOHOL

VITAL HP

ACTIVE INGREDIENT

ACTIVE INGREDIENTS: Arsenicum Album 30C, Cadmium Sulphuricum 30C, Calcarea Carbonica 30C, Carcinosinum 30C, Conium Maculatum 30C, Lycopodium Clavatum 30C, Medorrhinum 30C, Phytolacca Decandra 30C, Psorinum 30C, Sulphur 30C, Syphilinum 30C, Thuja Occidentalis 30C

PURPOSE

USES: Temporarily relieves exhaustion, glandular swellings, weakness, icy coldness, trembling, congestion, sleeplessness, &/or other symptoms associated with loss of vitality.

KEEP OUT OF REACH OF CHILDREN

KEEPT OF OF THE REACH OF CHILDREN. In case of overdose (or accidental ingestion) get medical help or contact a Poison Control Center.

INDICATIONS AND USAGE

USES: Temporarily relieves exhaustion, glandular swellings, weakness, icy coldness, trembling, congestion, sleeplessness, &/or other symptoms associated with loss of vitality.

WARNING:

Consult a physician for use inchildren under 12 years of age. IF PREGNANT OR BREAST-FEEDING, ask a health care professional before use. KEEP OUT OF THE REACH OF CHILDREN. In case of overdose (or accidental ingestion) get medical help or contact a Poison Control Center right away.

DOSAGE AND ADMINISTRATION

DIRECTIONS: Adults and children above 12 years: 10 drops orally 3 times daily, or as directed by a health care professional.

INACTIVE INGREDIENTS: Purified Water, USP Ethanol Alcohol 20%

PACKAGE LABEL

NDC: 43406-0108-1

VITAL HP

Loss Of Vitality

HOMEOPATHIC

1 fl oz (30 mL) / 20% Alcohol

UPC: 877730003119